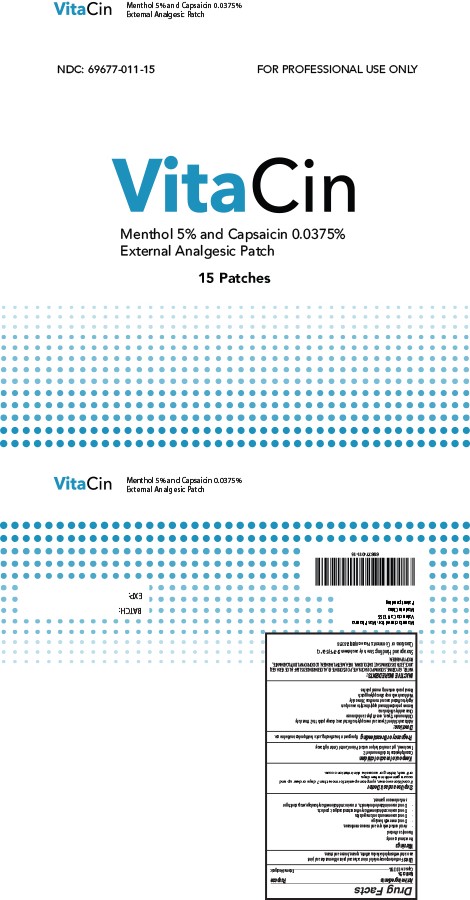 DRUG LABEL: Menthol, Capsaicin
NDC: 69677-011 | Form: PATCH
Manufacturer: MAS Management Group Inc.
Category: otc | Type: HUMAN OTC DRUG LABEL
Date: 20160830

ACTIVE INGREDIENTS: CAPSAICIN 0.375 mg/1 g; MENTHOL 50 mg/1 g
INACTIVE INGREDIENTS: EDETATE DISODIUM; DIAZOLIDINYL UREA; WATER; GLYCERIN; METHYLPARABEN; PROPYLPARABEN

ACTIVE INGREDIENTS

Menthol 5%

PURPOSE

External Analgesic

USES

For the temporary relief of minor aches and pains of the muscles and joints associated with simple backache, arthritis, sprains, bruises and strains.

WARNINGS

- For external use only.
- Use only as directed.
- Avoid contact with eyes and mucous membranes.
- Do not cover with bandage.
- Do not use on wounds or damaged skin.
- Do not use in combination with any other external analgesic products.
- Do not use on irritated or broken skin, or use in combination with any bandage, wrap, stocking or similar device or garment.

Keep out of reach of children

Consult physician for children under 12.

If swallowed, get a medical help or contact Poison Control Center right away.

Pregnancy or Breast Feeding

If pregnant or breast-feeding, ask a health professional before use.

DIRECTIONS

- Adults and children 12 years and over apply to affected area; change patch 1 to 2 times daily.
- Children under 12years, consult physician before use
- Clean and dry affected area
- Remove protective film and apply directly to area of pain
- Apply to affected area not more than 3 times daily
- Wash hands with soap after applying patch
- Reseal pouch containing unused patches

INACTIVE INGREDIENTS

WATER, GLYCERINE, SODIUM POLYACRYLATE, POLYSORBATE 80, ALOE BARBADESIS LEAF (ALOE VERA
GEL) JUICE, EDTA DISODIUM SALT, DIAZOLIDINYL UREA, METHYLPARABEN, LODOPROYNYL BUTYLCABAMATE, PROPYLPARABEN.

Storage and Handling

Store in dry area between 59-79 F(15-26 C)

Questions or Comments

Please call (800) 768-3518

DOSAGE AND ADMINISTRATION

Adults and children 12 years and over apply to affected area; change patch 1 to 2 times daily.

Children under 12years, consult physician before use.